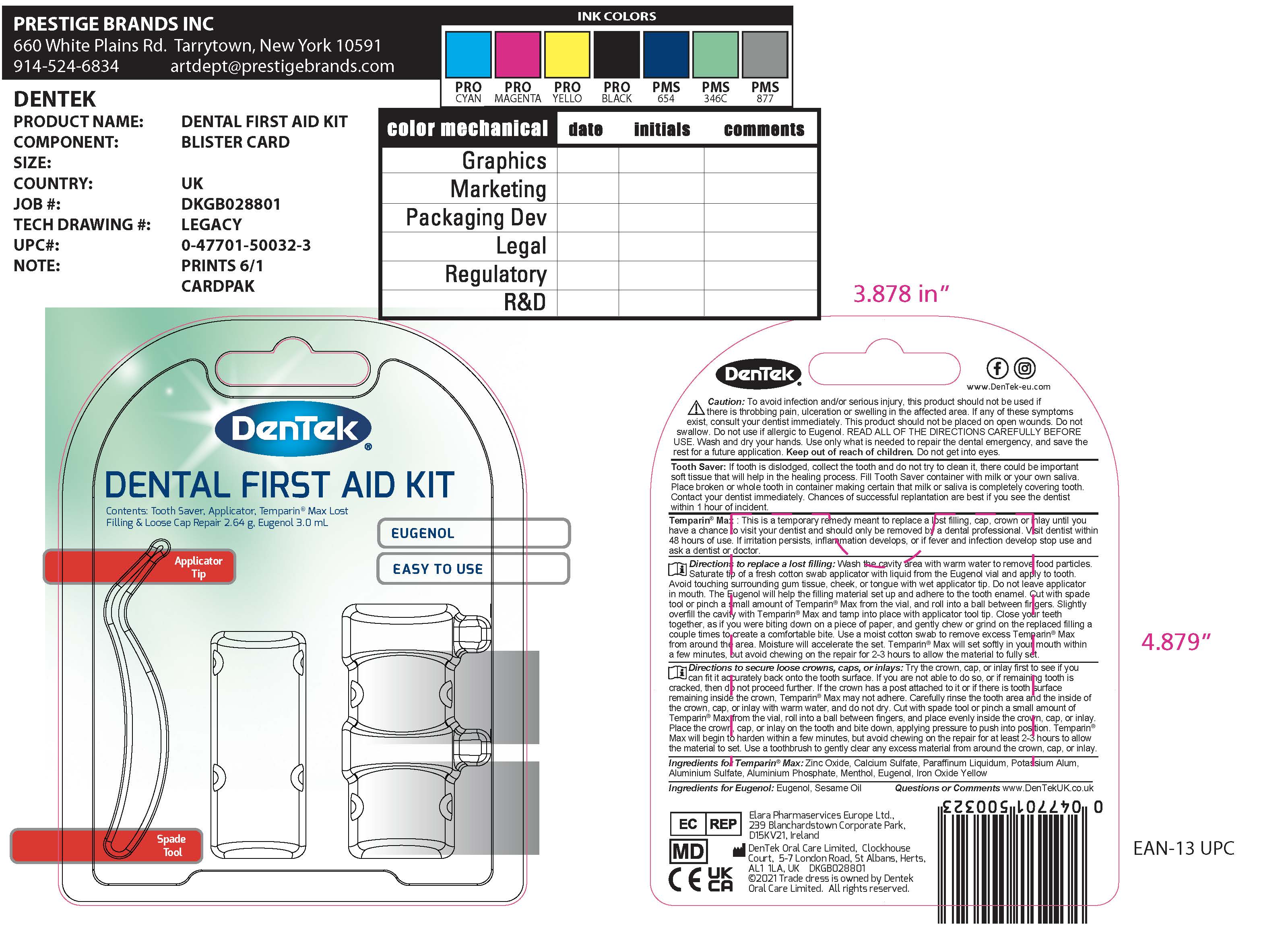 DRUG LABEL: DenTek Eugenol
NDC: 83062-400 | Form: LIQUID
Manufacturer: IIMED MEDICAL MEXICANA S. DE R.L. DE C.V.
Category: otc | Type: HUMAN OTC DRUG LABEL
Date: 20221010

ACTIVE INGREDIENTS: EUGENOL 850 mg/1 mL
INACTIVE INGREDIENTS: SESAME OIL 150 mg/1 mL

DenTek Dental First Aid Kit

Active ingredient

Eugenol 85%

Purpose

Toothache Relief Agent

Uses

For the temporary relief of throbbing, persisitent toothache due to a cavity. Visit Dentist within 48 hours of use.

Warnings

Allergy alert: do not use if you are allergic to eugenol (clove oil).

When using this product

- use only in teeth with persistent throbbing pain
- avoid touching tissuers other than tooth cavity
- DO NOT SWALLOW to avoid irritation
- avoid contact with eyes.

Do not use

- for more than 7 days
- more than the recommended dosage.

Stop use and ask a dentist or doctor if

- irritation persists
- inflammation develops
- if fever and infection develop.

Keep out of reach of children

If swallowed, get medical help or contact a Poison Control Center right away.

Directions

Directions Adults and children 12 year of age and older: Rinse the tooth with water to remove any food particles from the cavity. Moisten a cotton swab with Eugenol and place in the cavity for approximately 1 minute. Avoid touching tissue other than the tooth cavity. Apply the dose not more than four times daily or as directed by dentist or physician.

Adults and children 12 years and older use up to 4 times daily or as directed by a dentist or doctor.

Children under 12 years ask a dentist or doctor.

Inactive ingredient

sesame oil

Other information

- Do not purchase if package has been opened
- Store at 68-77 o F
- Cap tightly to avoid evaporation.